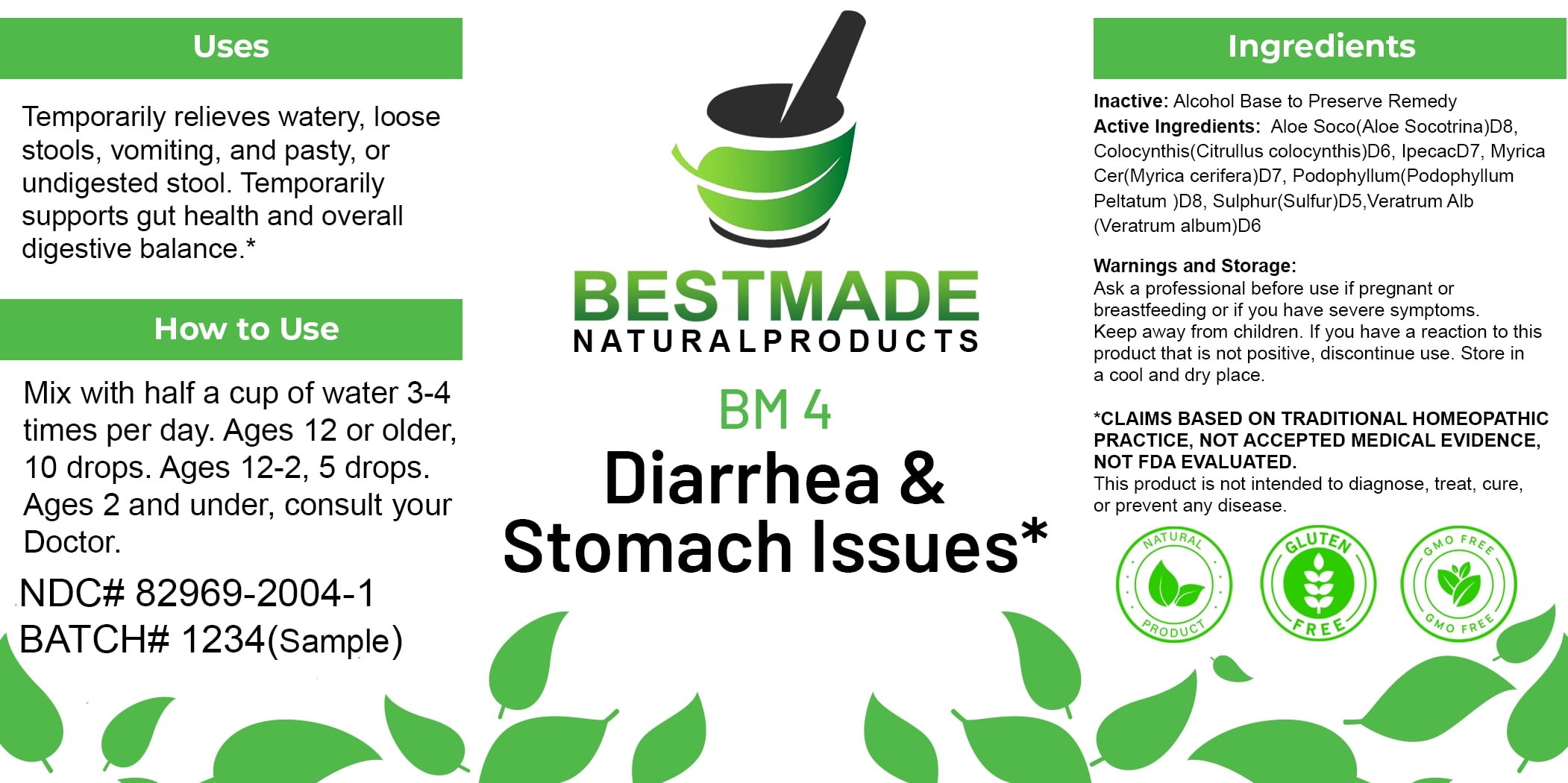 DRUG LABEL: Bestmade Natural Products BM4
NDC: 82969-2004 | Form: LIQUID
Manufacturer: Bestmade Natural Products
Category: homeopathic | Type: HUMAN OTC DRUG LABEL
Date: 20250122

ACTIVE INGREDIENTS: IPECAC 30 [hp_C]/30 [hp_C]; PODOPHYLLUM 30 [hp_C]/30 [hp_C]; CITRULLUS COLOCYNTHIS FRUIT PULP 30 [hp_C]/30 [hp_C]; ALOE 30 [hp_C]/30 [hp_C]; MORELLA CERIFERA ROOT BARK 30 [hp_C]/30 [hp_C]; SULFUR 30 [hp_C]/30 [hp_C]; VERATRUM ALBUM ROOT 30 [hp_C]/30 [hp_C]
INACTIVE INGREDIENTS: ALCOHOL 30 [hp_C]/30 [hp_C]

BM4

DOSAGE AND ADMINISTRATION

How to Use
Mix with half a cup of water 3-4 times per day. Ages 12 or older, 10 drops. Ages 12-2, 5 drops. Ages 2 and under, consult your Doctor.

Inactive:

Alcohol Base to Preserve Product

INDICATIONS AND USAGE

Temporarily relieves watery, loose stools, vomiting, and pasty, or undigested stool. Temporarily supports gut health and overall digestive balance.*

*Claims Based on Traditional Homeopathic Practice, Not Accepted Medical Evidence, Not FDA Evaluated.
This product is not intended to diagnose, treat, cure, or prevent any disease.

Active Ingredients:

Aloe Soco (Aloe Socotrina)D8, Colocynthis (Citrullus colocynthis)D6, IpecacD7, Myrica Cer (Myrica cerifera)D7, Podophyllum (Podophyllum Peltatum) JD8, Sulphur (Sulfur)D5, Veratrum Alb (Veratrum album)D6

KEEP OUT OF REACH OF CHILDREN

Warnings and Storage:

Ask a professional before use if pregnant or breastfeeding or if you have severe symptoms. Keep away from children. If you have a reaction to this product that is not positive, discontinue use. Store in a cool and dry place.

PURPOSE

Temporarily relieves watery, loose stools, vomiting, and pasty, or undigested stool. Temporarily supports gut health and overall digestive balance.*

*Claims Based on Traditional Homeopathic Practice, Not Accepted Medical Evidence, Not FDA Evaluated.
This product is not intended to diagnose, treat, cure, or prevent any disease.

Warnings and Storage:

Ask a professional before use if pregnant or breastfeeding or if you have severe symptoms. Keep away from children. If you have a reaction to this product that is not positive, discontinue use. Store in a cool and dry place.

Claims Based on Traditional Homeopathic Practice, Not Accepted Medical Evidence, Not FDA Evaluated.

This product is not intended to diagnose, treat, cure, or prevent any disease.

Entire package label